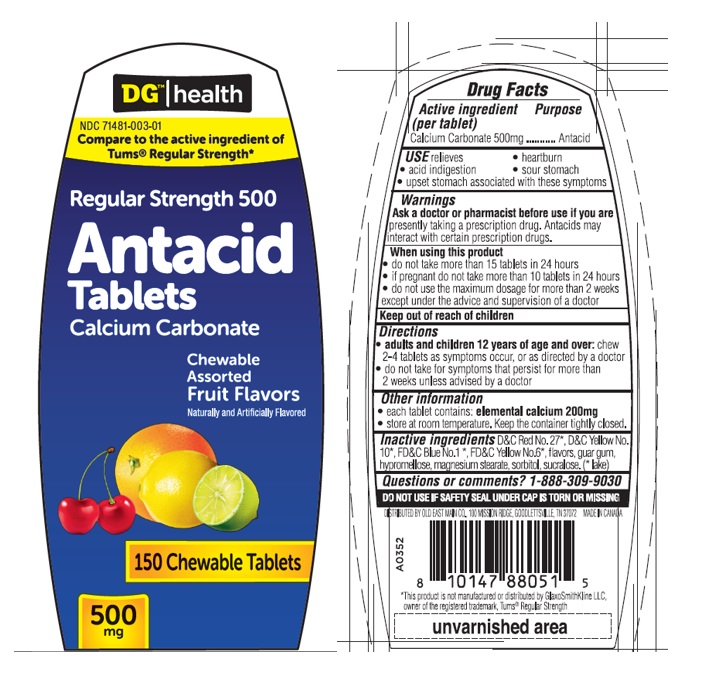 DRUG LABEL: DGH Antacid Regular Strength 500 (Fruit assorted), 150ct
NDC: 71481-003 | Form: TABLET
Manufacturer: BioV Health Inc
Category: otc | Type: HUMAN OTC DRUG LABEL
Date: 20240404

ACTIVE INGREDIENTS: CALCIUM CARBONATE 500 mg/1 1
INACTIVE INGREDIENTS: D&C RED NO. 27; D&C YELLOW NO. 10 ALUMINUM LAKE; FD&C BLUE NO. 1 ALUMINUM LAKE; FD&C YELLOW NO. 6; GUAR GUM; HYPROMELLOSE, UNSPECIFIED; MAGNESIUM STEARATE; SORBITOL; SUCRALOSE

DGH Antacid Regular Strength 500 (Fruit assorted)

Active ingredient (per tablet)

Calcium Carbonate 500mg

Purpose

Antacid

USE

Relieves • acid indigestion • heartburn • sour stomach • upset stomach associated with these symptoms

Warnings

Ask a doctor or pharmacist before use if you arepresently taking a prescription drug. Antacids may interact with certain prescription drugs.

When using this product

- do not take more than 15 tablets in 24 hours.
- if pregnant do not take more than 10 tablets in 24 hours.
- do not use the maximum dosage for more than 2 weeks except under the advice and supervision of a doctor.

Keep out of of reach of children

Directions

- adults and children 12 years of age and over:chew 2-4 tablets as symtoms occur, or as directed by a doctor
- do not take for symtoms that persist for more than 2 weeks unless advised by a doctor

Other information

each tablet contains: elemental calcium 200 mg.

Store at room temperature. Keep the container tightly closed.

Inactive ingredients

D&C Red No.27*, D&C Yellow No.10*, FD&C Blue No.1*, FD&C Yellow No.6*, flavors, guar gum, hypromellose, magnesium stearate, sorbitol, sucralose. (* lake)

Questions or comments?

1-888-309-9030